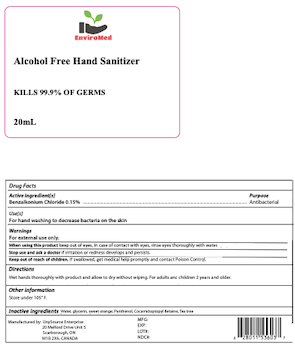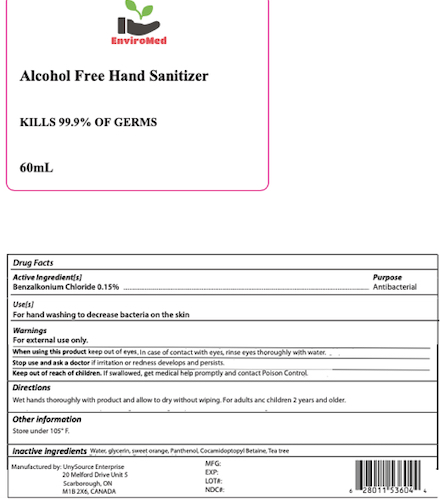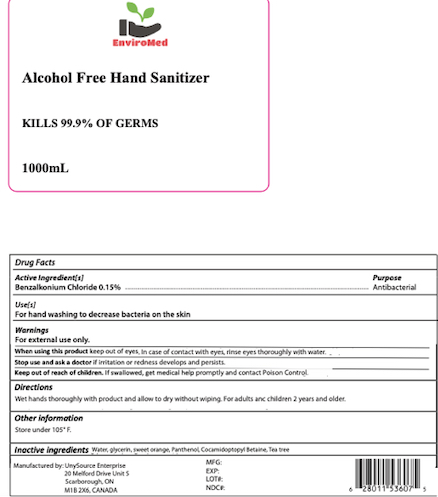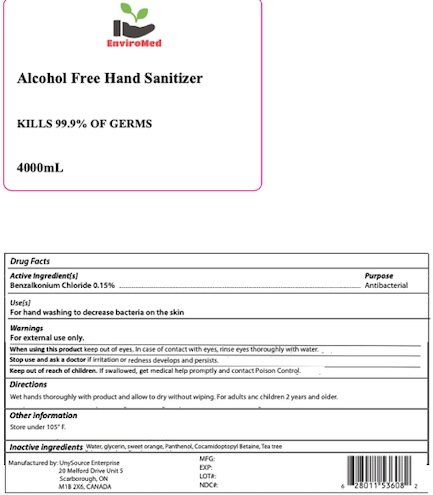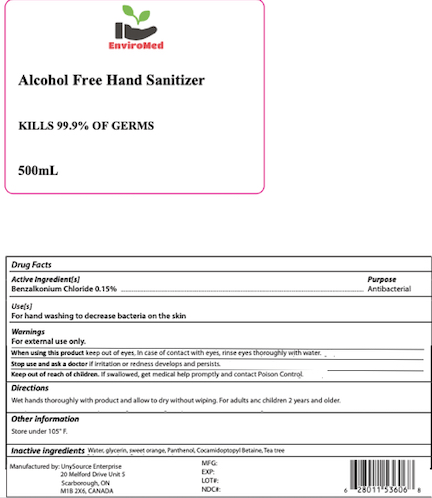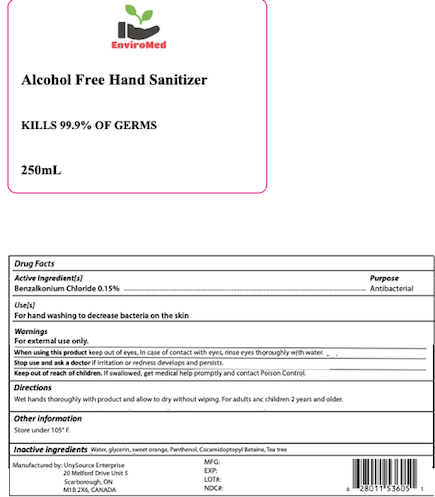 DRUG LABEL: Enviromed Hand Sanitizer
NDC: 79505-012 | Form: SOLUTION
Manufacturer: Unysource Enterprise
Category: otc | Type: HUMAN OTC DRUG LABEL
Date: 20201210

ACTIVE INGREDIENTS: BENZALKONIUM CHLORIDE 0.0015 g/1 mL
INACTIVE INGREDIENTS: TEA TREE OIL; ORANGE OIL; PANTHENOL; COCAMIDOPROPYL BETAINE; GLYCERIN; WATER

Enviromed Hand Sanitizer Alcohol free

DRUG FACTS

Active Ingredient

Benzalkonium chloride 0.15%

Purpose

Antiseptic

Uses

For hand sanitizing. To decrease bacteria on the skin.

Warnings

For external use only.

Do not use in the eyes.

In case of eye contact, rinse eyes thoroughly with water.

Stop use and ask a doctor

if irritation or redness develops, or if condition persists more than 72 hours.

Keep out of reach of children.

Instruct children on proper use. If swallowed, get medical help or contact a Poison Control Center right away.

Directions

Apply small amount to wetted hands and wash vigorously for 15 seconds, make sure to get between fingers and under finger nails. Rinse with warm, clean water. Repeat as necessary.

Inactive Ingredients

Tea tree oil, Cocamidopropyl Betaine, Sweet Orange, Glycerin, Panthenol, Water

Purpose

Antiseptic

Uses

For hand sanitizing. To decrease bacteria on the skin.

Warnings

For external use only.

Do Not Use

In case of eye contact, rinse eyes thoroughly with water.

Stop Use Ask a Doctor

if irritation or redness develops, or if condition persists more than 72 hours.

Keep Out of Reach of Children

Instruct children on proper use. If swallowed, get medical help or contact a Poison Control Center right away.

Directions

Apply small amount to wetted hands and wash vigorously for 15 seconds, make sure to get between fingers and under finger nails. Rinse with warm, clean water. Repeat as necessary.

Inactive Ingredients

Tea tree oil, Cocamidopropyl Betaine, Sweet Orange, Glycerin, Panthenol, Water

Purpose

Antiseptic

Uses

For hand sanitizing. To decrease bacteria on the skin.

Warnings

For external use only.

Do Not Use

In case of eye contact, rinse eyes thoroughly with water.

Stop Use Ask a Doctor

if irritation or redness develops, or if condition persists more than 72 hours.

Keep Out of Reach of Children

Instruct children on proper use. If swallowed, get medical help or contact a Poison Control Center right away.

Directions

Apply small amount to wetted hands and wash vigorously for 15 seconds, make sure to get between fingers and under finger nails. Rinse with warm, clean water. Repeat as necessary.

Inactive Ingredients

Tea tree oil, Cocamidopropyl Betaine, Sweet Orange, Glycerin, Panthenol, Water

Purpose

Antiseptic

Uses

For hand sanitizing. To decrease bacteria on the skin.

Warnings

For external use only.

Do not Use

In case of eye contact, rinse eyes thoroughly with water.

Stop Use Ask a Doctor

if irritation or redness develops, or if condition persists more than 72 hours.

Keep Out of Reach of Children

Instruct children on proper use. If swallowed, get medical help or contact a Poison Control Center right away.

Directions

Apply small amount to wetted hands and wash vigorously for 15 seconds, make sure to get between fingers and under finger nails. Rinse with warm, clean water. Repeat as necessary.

Inactive Ingredients

Tea tree oil, Cocamidopropyl Betaine, Sweet Orange, Glycerin, Panthenol, Water

Purpose

Antiseptic

Uses

For hand sanitizing. To decrease bacteria on the skin.

Warnings

For External Use only

Do not Use

In case of eye contact, rinse eyes thoroughly with water.

Stop Use and Ask a Doctor

if irritation or redness develops, or if condition persists more than 72 hours.

Keep out of Reach of Children

Instruct children on proper use. If swallowed, get medical help or contact a Poison Control Center right away.

Directions

Apply small amount to wetted hands and wash vigorously for 15 seconds, make sure to get between fingers and under finger nails. Rinse with warm, clean water. Repeat as necessary.

Inactive Ingredients

Tea tree oil, Cocamidopropyl Betaine, Sweet Orange, Glycerin, Panthenol, Water

Purpose

Antiseptic

Uses

For hand sanitizing. To decrease bacteria on the skin.

Warnings

For external use only.

Do not Use

In case of eye contact, rinse eyes thoroughly with water.

Stop Use and Ask a Doctor

if irritation or redness develops, or if condition persists more than 72 hours.

Keep out of Reach of Children

Instruct children on proper use. If swallowed, get medical help or contact a Poison Control Center right away.

Directions

Apply small amount to wetted hands and wash vigorously for 15 seconds, make sure to get between fingers and under finger nails. Rinse with warm, clean water. Repeat as necessary.

Inactive Ingredients

Tea tree oil, Cocamidopropyl Betaine, Sweet Orange, Glycerin, Panthenol, Water

PRINCIPAL DISPLAY PANEL

20ml NDC 79505-012-01

PRINCIPAL DISPLAY PANEL

60ml NDC 79505-012-02

Principal Display Panel

250 ml NDC 79505-012-03

Principal Display Panel

500 mL NDC 79505-012-04

Principal Display Panel

1000ml NDC 79505-012-05

Principal Display Panel

4000 mL NDC 79505-012-06